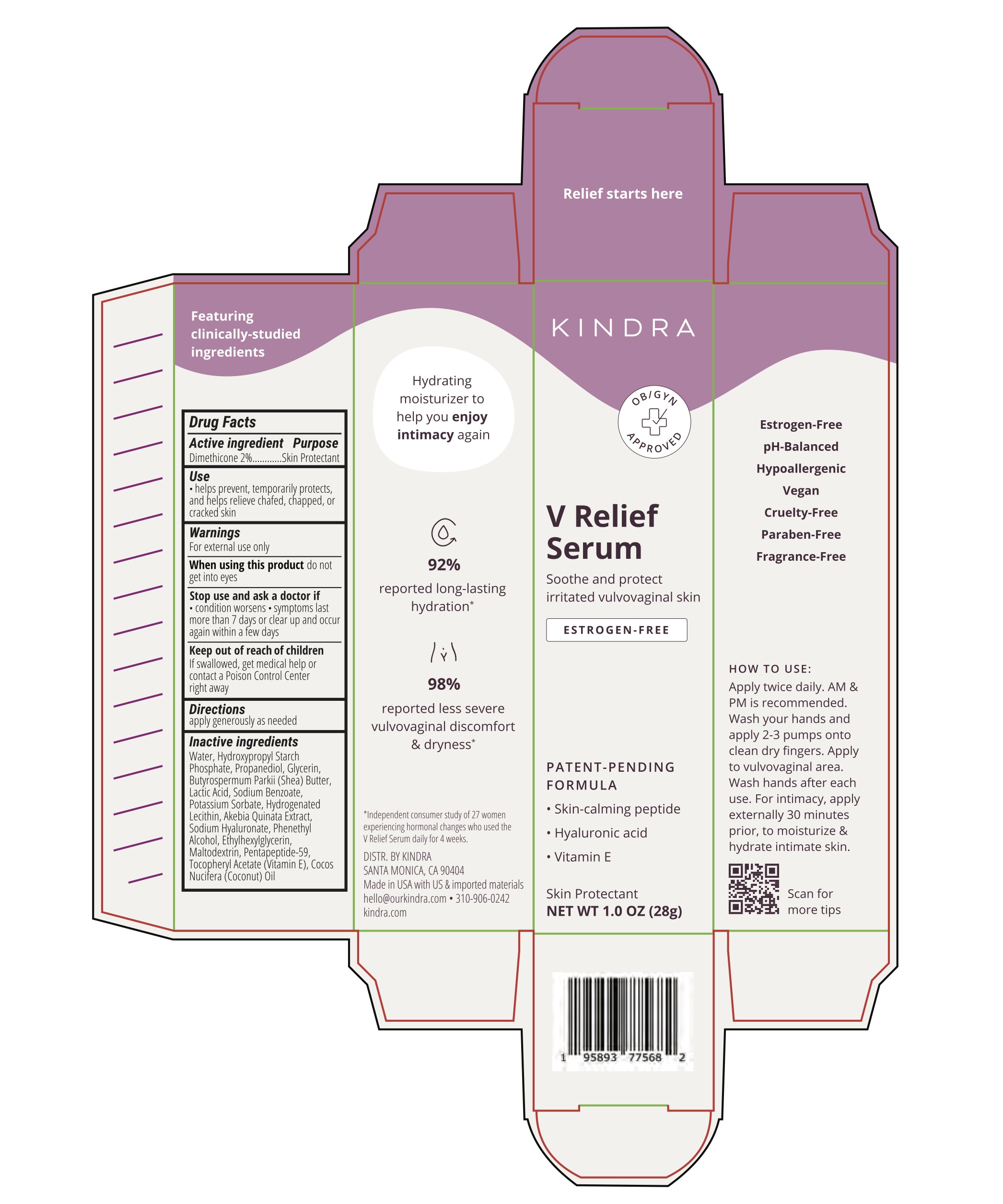 DRUG LABEL: V Relief Serum
NDC: 84528-682 | Form: GEL
Manufacturer: Kindra
Category: otc | Type: HUMAN OTC DRUG LABEL
Date: 20260108

ACTIVE INGREDIENTS: DIMETHICONE 0.56 g/28 g
INACTIVE INGREDIENTS: SHEA BUTTER; LACTIC ACID; SODIUM BENZOATE; HYDROGENATED SOYBEAN LECITHIN; MALTODEXTRIN; WATER; GLYCERIN; HYALURONATE SODIUM; ALPHA-TOCOPHEROL ACETATE; PHENYLETHYL ALCOHOL; PROPANEDIOL; POTASSIUM SORBATE; ETHYLHEXYLGLYCERIN; COCONUT OIL; PENTAPEPTIDE-59

Active ingredient

Dimethicone 2%

Purpose

Skin Protectant

Use

- helps prevent, temporarily protects, and helps relieve chafed, chapped, or cracked skin

Warnings

For external use only

When using this product do not get into eyes

Stop use and ask a doctor if

- condition worsens
- symptoms last more than 7 days or clear up and occur again within a few days

Keep out of reach of children. If swallowed, get medical help or contact a Poison Control Center right away

Directions

apply generously as needed

Inactive ingredients

Water, Hydroxypropyl Starch Phosphate, Propanediol, Glycerin, Butyrospermum Parkii (Shea) Butter, Lactic Acid, Sodium Benzoate, Potassium Sorbate, Hydrogenated Lecithin, Akebia Quinata Extract, Sodium Hyaluronate, Phenethyl Alcohol, Ethylhexylglycerin, Maltodextrin, Pentapeptide-59, Tocopheryl Acetate (Vitamin E), Cocos Nucifera (Coconut) Oil

Questions?

310-906-0242

hello@ourkindra.com

DISTR. BY KINDRA

SANTA MONICA, CA 90404

Made in USA with US & imported materials

PRINCIPAL DISPLAY PANAL

KINDRA

V Relief Serum

Soothe and protect irritated vulvovaginal skin

ESTROGEN-FREE

PATENT-PENDING FORMULA:

- Skin-calming peptide
- Hyaluronic acid
- Vitamin E

Skin Protectant

NET WT 1.0 OZ (28g)